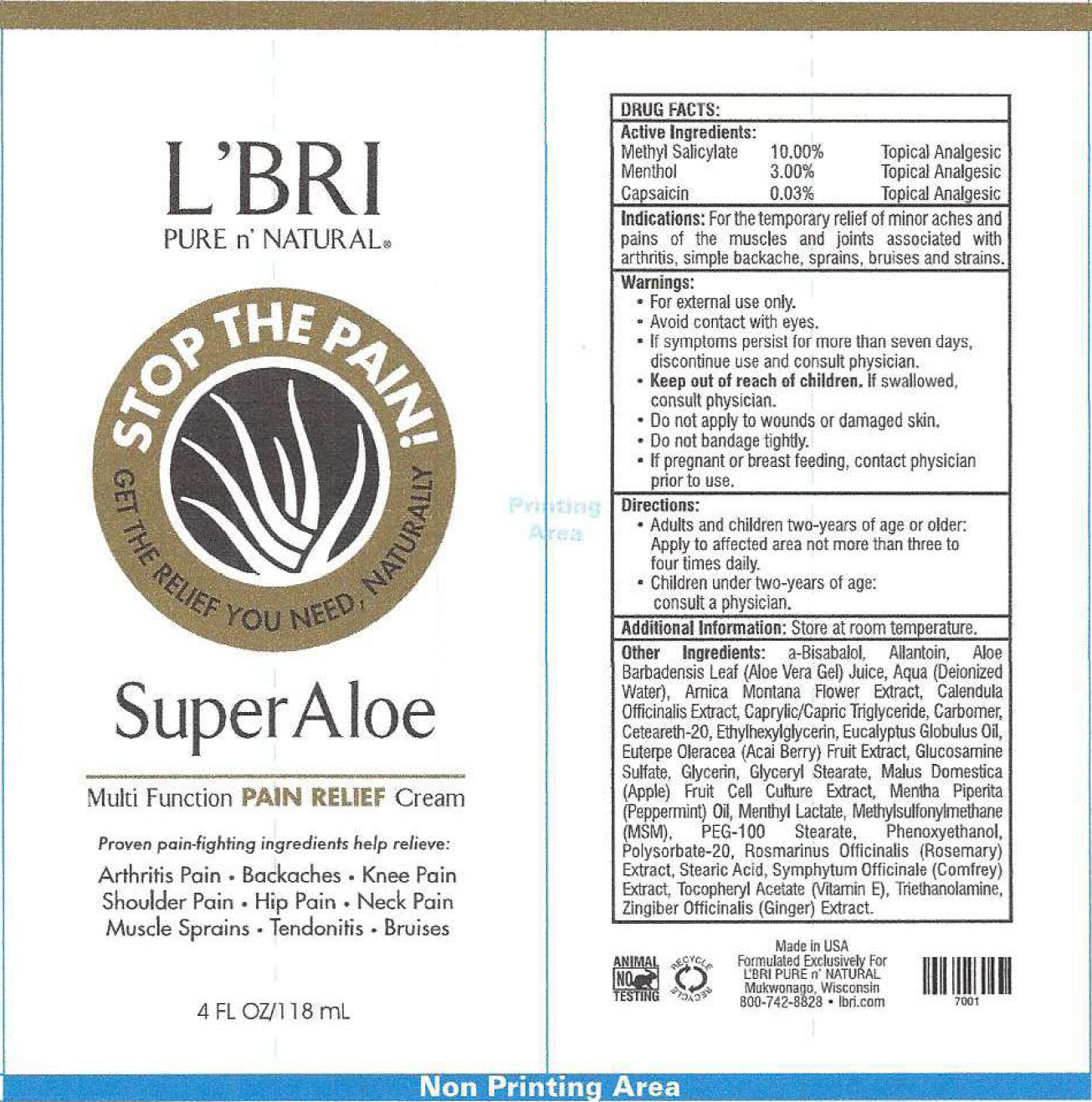 DRUG LABEL: LBri Super Aloe Stop The Pain
NDC: 71238-847 | Form: CREAM
Manufacturer: L'Bris, Pure 'N Natural
Category: otc | Type: HUMAN OTC DRUG LABEL
Date: 20231111

ACTIVE INGREDIENTS: METHYL SALICYLATE 100 mg/1 mL; MENTHOL 30 mg/1 mL; CAPSAICIN 0.3 mg/1 mL
INACTIVE INGREDIENTS: ALLANTOIN; ALOE VERA LEAF; WATER; ARNICA MONTANA FLOWER; CALENDULA OFFICINALIS FLOWER; MEDIUM-CHAIN TRIGLYCERIDES; CARBOXYPOLYMETHYLENE; POLYOXYL 20 CETOSTEARYL ETHER; ETHYLHEXYLGLYCERIN; EUCALYPTUS OIL; GLUCOSAMINE SULFATE; GLYCERIN; GLYCERYL MONOSTEARATE; APPLE; PEPPERMINT OIL; METHYL LACTATE, (-)-; DIMETHYL SULFONE; PEG-100 STEARATE; PHENOXYETHANOL; POLYSORBATE 20; ROSEMARY; STEARIC ACID; SYMPHYTUM UPLANDICUM LEAF; .ALPHA.-TOCOPHEROL ACETATE; TROLAMINE; GINGER

L'Bri Super Aloe Stop The Pain

Active Ingredients:

Methyl Salicylate 10.00%

Menthol 3.00%

Capsaicin 0.03%

PURPOSE

Topical Analgesic

Indications:

For the temporary relief of minor aches and pains of the muscles and joints associated with arthritis, simple backache, sprains, bruises and strains.

Warnings:

- For external use only.
- Avoid contact with eyes.
- If symptoms persist for more than seven days, discontinue use and consult physician.

Keep out of reach of children.

- If swallowed, consult physician.
- Do not apply to wounds or damaged skin.
- Do not bandage tightly.

If pregnant or breast feeding,

contact physician prior to use.

Directions:

- Adults and children two-years of age or older: Apply to affected area not more than three to four times daily.
- Children under two-years of age: consult a physician.

Additional Information:

Store at room temperature.

Other Ingredients:

a-Bisabalol, Allantoin, Aloe Barbadensis Leaf (Aloe Vera Gel) Juice, Aqua (Deionized Water) Arnica Montana Flower Extract, Calendula Officinalis Extract, Caprylic/Capric Triglyceride, Carbomer, Ceteareth-20, Ethylhexylglycerin, Eucalyptus Globulus Oil, Euterpe Oleracea (Acai Berry) Fruit Extract, Glucosaminine Sulfate, Glycerin, Glyceryl Stearate, Malus Domestica (Apple) Fruit Cell Culture Extract, Mentha Piperita (Peppermint) Oil, Methyl Lactate, Methylsulfonylmethane (MSM), PEG-100 Stearate, Phenoxyethanol, Polysorbate-20, Rosmarinus Officinalis (Rosemary) Extract, Stearic Acid, Symphytum Officinale (Comfrey) Extract, Tocopheryl Acetate (Vitamin E), Triethanolamine, Zingiber Officinalis (Ginger) Extract.